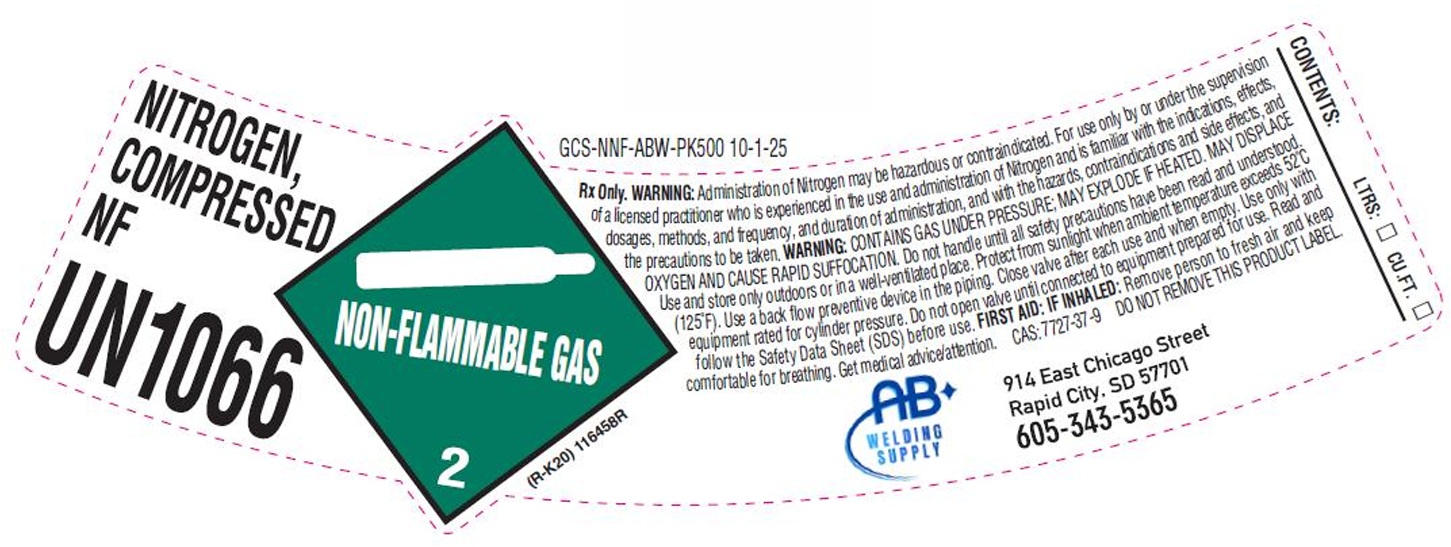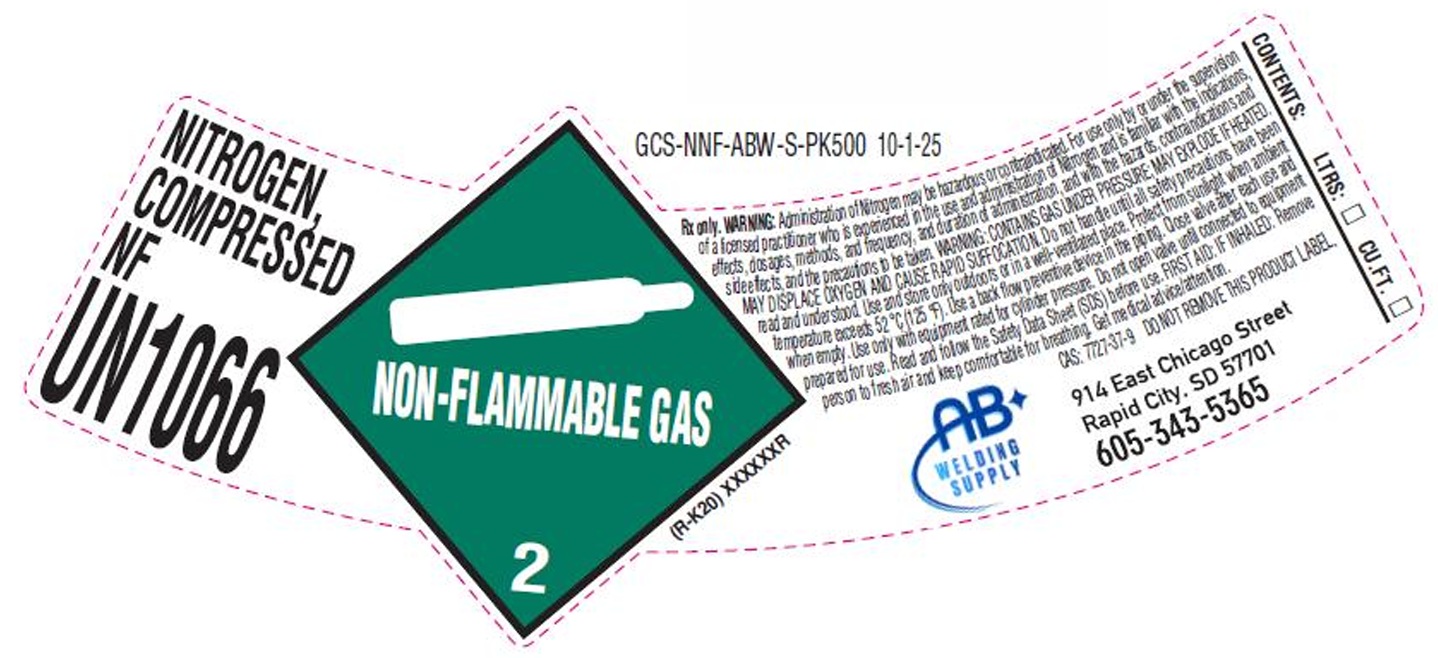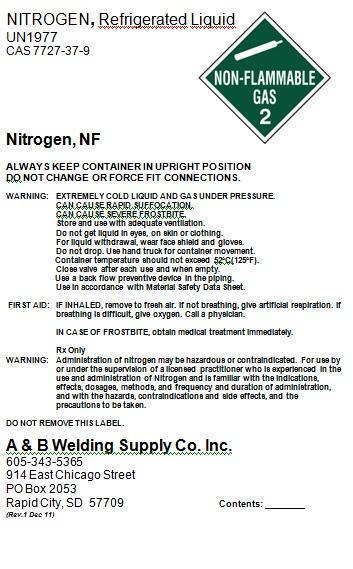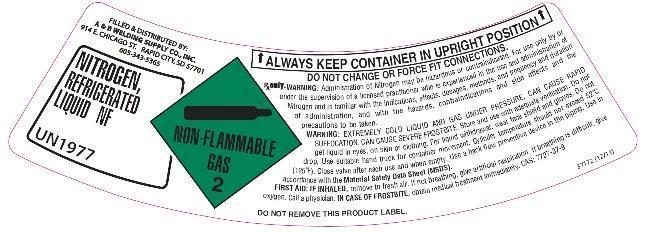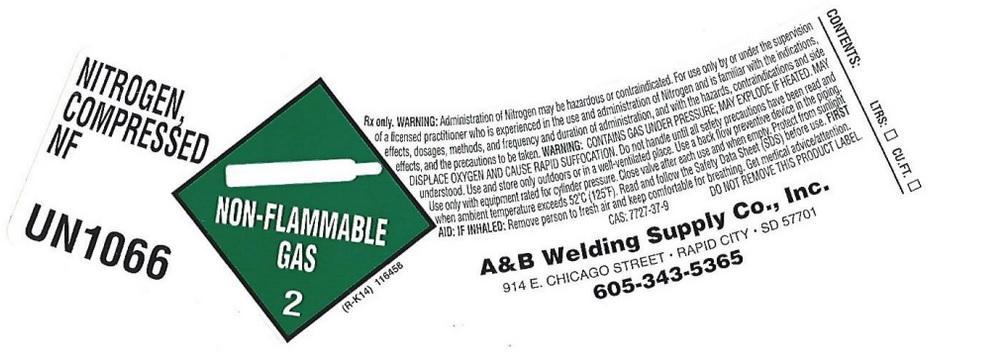 DRUG LABEL: Nitrogen
NDC: 55728-012 | Form: GAS
Manufacturer: A&B Welding Supply, LLC
Category: animal | Type: PRESCRIPTION ANIMAL DRUG LABEL
Date: 20251118

ACTIVE INGREDIENTS: Nitrogen 990 mL/1 L

Nitrogen

PACKAGE LABEL

NITROGEN, Refrigerated Liquid
UN1977
CAS 7727-37-9
NON-FLAMMABLE GAS 2

Nitrogen, NF

ALWAYS KEEP CONTAINER IN UPRIGHT POSITION
DO NOT CHANGE OR FORCE FIT CONNECTIONS.

WARNING: EXTREMELY COLD LIQUID AND GAS UNDER PRESSURE.
CAN CAUSE RAPID SUFFOCATION.
CAN CAUSE SEVERE FROSTBITE.
Store and use with adequate ventilation.
Do not get liquid in eyes, on skin or clothing.
For liquid withdrawal, wear face shield and gloves.
Do not drop. Use hand truck for container movement.
Container temperature should not exceed 52oC(125oF).
Close valve after each use and when empty.
Use a back flow preventive device in the piping.
Use in accordance with Material Safety Data Sheet.

FIRST AID: IF INHALED, remove to fresh air. If not breathing, give artificial respiration. If breathing is difficult, give oxygen. Call a physician.

IN CASE OF FROSTBITE, obtain medical treatment immediately.

Rx Only
WARNING: Administration of nitrogen may be hazardous or contraindicated. For use by or under the supervision of a licensed practitioner who is experienced in the use and administration of Nitrogen and is familiar with the indications, effects, dosages, methods, and frequency and duration of administration, and with the hazards, contraindications and side effects, and the precautions to be taken.

DO NOT REMOVE THIS LABEL.

A and B Welding Supply Co. Inc.
605-343-5365
914 East Chicago Street
PO Box 2053
Rapid City, SD 57709 Contents:

PACKAGE LABEL

NITROGEN, COMPRESSED NF
UN 1066
NON-FLAMMABLE GAS 2
Rx only. WARNING: Administration of Nitrogen may be hazardous or contraindicated. For use only by or under the supervision of a licensed practitioner who is experienced in the use and administration of Nitrogen and is familiar with the indications, effects, dosages, methods, and frequency and duration of administration, and with the hazards, contraindications and side effects, and precautions to be taken. WARNING: CONTAINS GAS UNDER PRESSURE; MAY EXPLODE IF HEATED. MAY DISPLACE OXYGEN AND CAUSE RAPID SUFFOCATION. Do not handle until all safety precautions have been read and understood. Use and store only outdoors or in a well-ventilated place. Use a back flow preventive device in the piping. Use only with equipment rated for cylinder pressure. Close valve after each use and when empty. Protect from sunlight when ambient temperature exceed 52 degrees C (125 degrees F). Read and follow the Safety Data Sheet (SDS) before use. FIRST AID: IF INHALED: Remove person to fresh air and keep comfortable for breathing. Get medical advice/attention. CAS: 7727-37-9
DO NOT REMOVE THIS PRODUCT LABEL.
A&B Welding Supply Co., Inc.
914 W Chicago Street
Rapid City, SD 57701
605-343-5365
CONTENTS: LTRS CU FT

PACKAGE LABEL

FILLED AND DISTRIBUTED BY:

A AND B WELDING SUPPLY CO., INC

914 E CHICAGO ST

RAPID CITY, SD 57701

605-343-5365

NITROGEN, REFRIGERATED LIQUID NF

UN 1977

NON-FLAMMABLE GAS 2

ALWAYS KEEP CONTAINER IN UPRIGHT POSITION

DO NOT CHANGE OR FORCE FIT CONNECTIONS

Rx only. WARNING: Administration of Nitrogen my be hazardous or contraindicated. For use only by or under the supervision of a licensed practitioner who is experienced in the use and administration of Nitrogen and is familiar with the indications, effects, dosages, methods, and frequency and duration of administration, and with the hazards, contraindications and side effects and the precautions to be taken.

WARNING: EXTREMELY COLD LIQUID AND GAS UNDER PRESSURE. CAN CAUSE RAPID SUFFOCATION. CAN CAUSE SEVERE FROSTBITE. Store and use with adequate ventilation. Do not get liquid in eyes, on skin or clothing. For liquid withdrawal, wear face shield and gloves. Do not drop. Use suitable hand truck for container movement. cylinder temperature should not exceed 52 degrees C (125 degrees F). Close valve after each use and when empty. Use a back flow preventive device in the piping. Use in accordance with the Material Safety Data Sheet (MSDS).

FIRST AID: IF INHALED, remove to fresh air. If not breathing, give artificial respiration. If breathing is difficult, give Oxygen. Call a physician. IN CASE OF FROSTBITE, obtain medical treatment immediately. CAS 7727-37-9

PACKAGE LABEL

NITROGEN, COMPRESSED NF
UN1066
Rx Only. WARNING: Administration of Nitrogen may be hazardous or contraindicated. For use only by or under the supervision of a licensed practitioner who is experienced in the use and administration of Nitrogen and is familiar with the indications, effects, dosages, methods, and frequency, and duration of administration, and with the hazards, contraindications and side effects, and the precautions to be taken. WARNING: CONTAINS GAS UNDER PRESSURE; MAY EXPLODE IF HEATED. MAY DISPLACE OXYGEN AND CAUSE RAPID SUFFOCATION. Do not handle until all safety precautions have been read and understood. Use and store only outdoors or in a well-ventilated place. Protect from sunlight when ambient temperature exceeds 52 C (125 F). Use a back flow preventive device in the piping. Close valve after each use and when empty. Use only with equipment rated for cylinder pressure. Do not open valve until connected to equipment prepared for use. Read and follow the Safety Data Sheet (SDS) before use. FIRST AID: IF INHALED: Remove person to fresh air and keep comfortable for breathing. Get medical advice/attention. CAS: 7727-37-9 DO NOT REMOVE THIS PRODUCT LABEL.
AB WELDING SUPPLY
914 East Chicago Street
Rapid City, SD 57701
605-674-7523
NO SMOKING
NO VAPING
CONTENTS: LTRS: CU.FT.